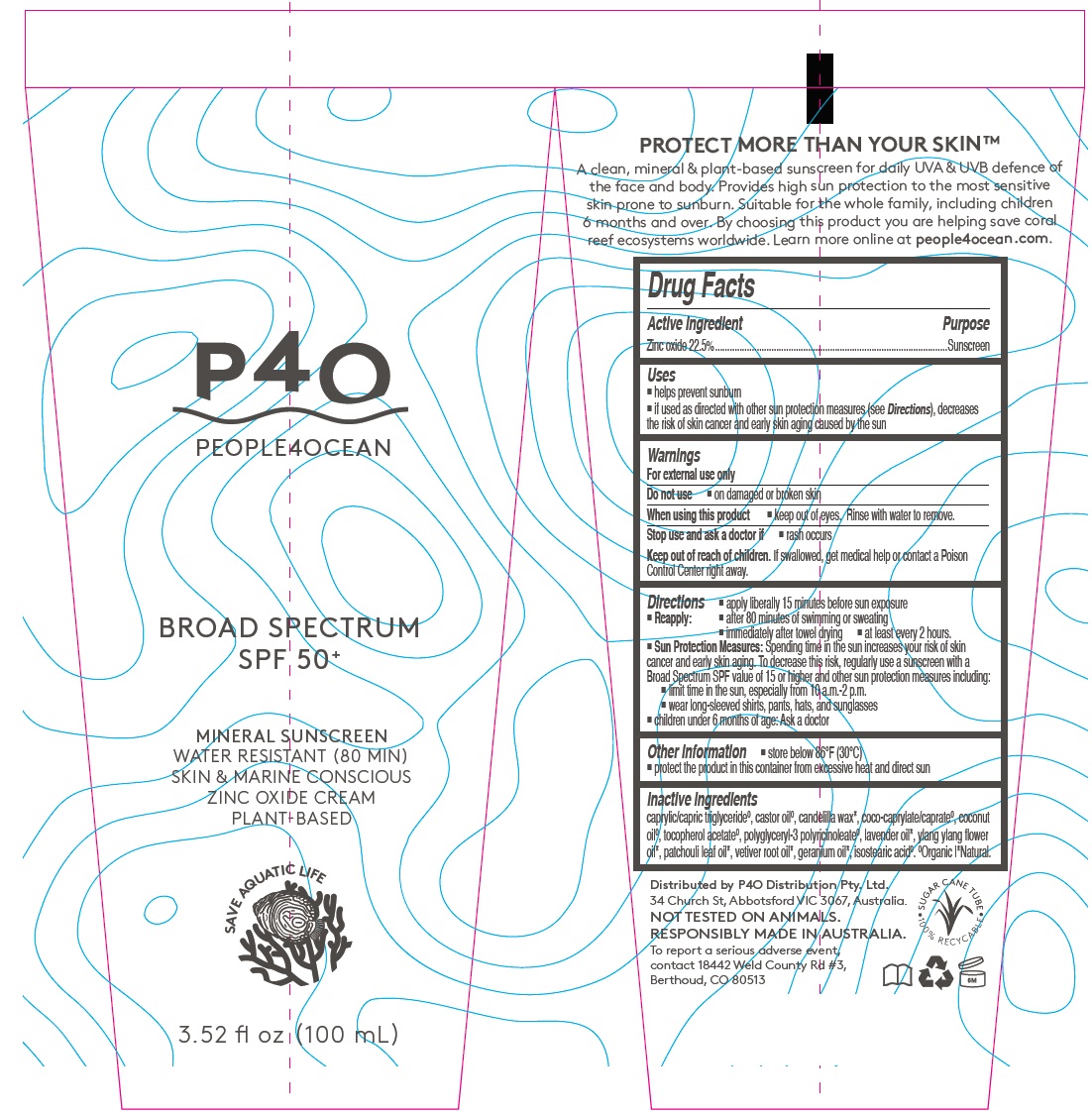 DRUG LABEL: People4Ocean SPF50 sunscreen vegan
NDC: 73192-020 | Form: CREAM
Manufacturer: P4O Distribution Pty Ltd
Category: otc | Type: HUMAN OTC DRUG LABEL
Date: 20200701

ACTIVE INGREDIENTS: ZINC OXIDE 225 mg/1 mL
INACTIVE INGREDIENTS: MEDIUM-CHAIN TRIGLYCERIDES; CASTOR OIL; CANDELILLA WAX; COCOYL CAPRYLOCAPRATE; COCONUT OIL; .ALPHA.-TOCOPHEROL ACETATE; POLYGLYCERYL-3 PENTARICINOLEATE; LAVENDER OIL; CANANGA OIL; GERANIUM OIL, ALGERIAN TYPE; ISOSTEARIC ACID

People4Ocean SPF50 sunscreen vegan

Active ingredient

Zinc oxide 22.5%

Purpose

Sunscreen

Uses

- helps prevent sunburn
- if used as directed with other sun protection measures (see Directions), decreases the risk of skin cancer and early skin aging caused by the sun

Warnings

For external use only

Do not use

- on damaged or broken skin

When using this product

keep out of eyes. Rinse with water to remove.

Stop use and ask a doctor if

rash occurs

Keep out of reach of children.

If swallowed, get medical help or contact a Poison Control Center right away.

Directions

- apply liberally 15 minutes before sun exposure
- Reapply:
- after 80 minutes of swimming or sweating
- immediately after towel drying
- at least every 2 hours.
- Sun Protection Measures: Spending time in the sun increases your risk of skin cancer and early skin aging. To decrease this risk, regularly use a sunscreen with a Broad Spectrum SPF value of 15 or higher and other sun protection measures including:
- limit time in the sun, especially from 10 a.m.-2 p.m.
- wear long-sleeved shirts, pants, hats, and sunglasses
- children under 6 months of age: Ask a doctor

Other information

- store below 86°F (30°C)
- protect the product in this container from excessive heat and direct sun

Inactive ingredients

caprylic/capric triglycerideº, castor oilº, candelilla wax*, coco-caprylate/caprateº, coconut oilº, tocopherol acetateº, polyglyceryl-3 polyricinoleateº, lavender oil*, ylang ylang flower oil*, patchouli leaf oil*, vetiver root oil*, geranium oil*, isostearic acidº. ºOrganic |*Natural.